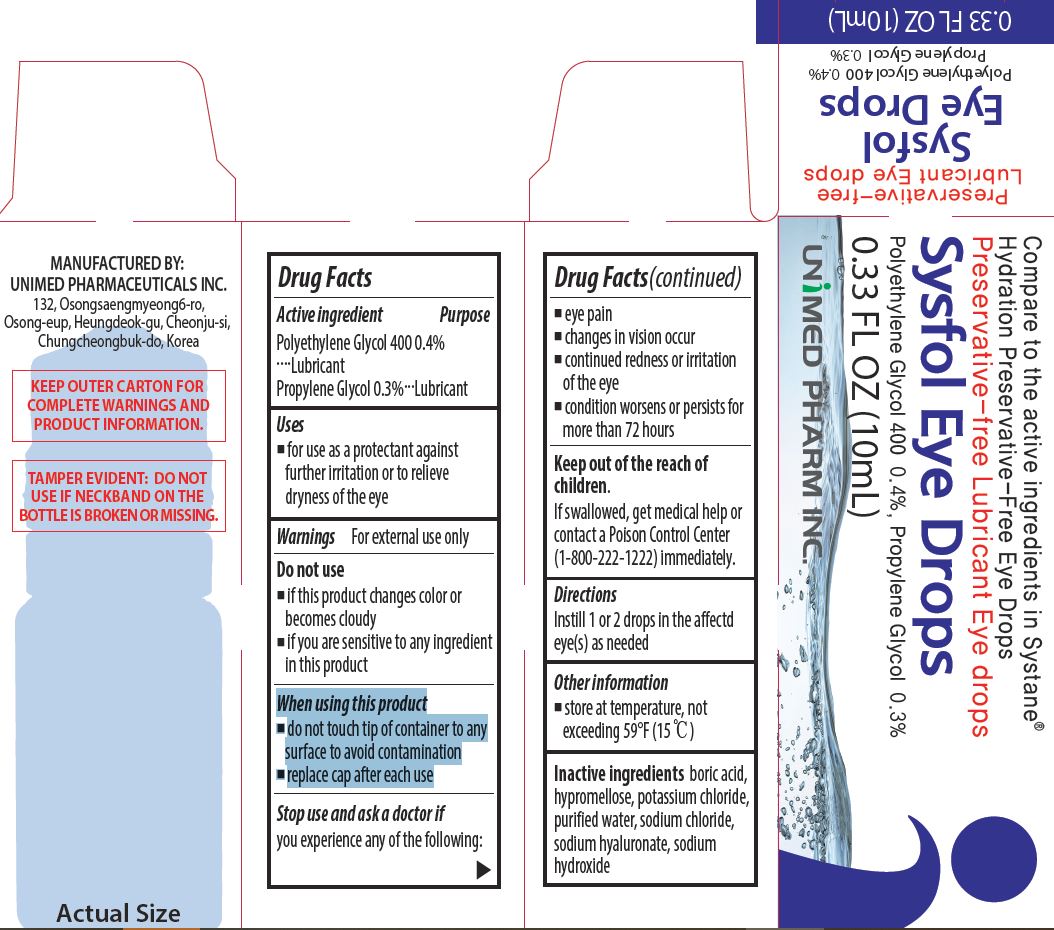 DRUG LABEL: Sysfol Eye Drops
NDC: 73669-013 | Form: LIQUID
Manufacturer: Unimed Pharmaceuticals, Inc.
Category: otc | Type: HUMAN OTC DRUG LABEL
Date: 20230510

ACTIVE INGREDIENTS: POLYETHYLENE GLYCOL 400 0.4 g/100 mL; PROPYLENE GLYCOL 0.3 g/100 mL
INACTIVE INGREDIENTS: WATER

Drug Facts

ACTIVE INGREDIENT

Polyethylene Glycol 400, Propylene Glycol

INACTIVE INGREDIENT

boric acid, hypromellose, potassium chloride, purified water, sodium chloride, sodium hyaluronate, sodium, hydroxide

PURPOSE

for use as a protectant against further irritation or to relieve dryness of the eye

keep out of reach of the children

INDICATIONS AND USAGE

Instill 1 or 2 drops in the affectd eye(s) as needed

WARNINGS

For external use only
When using this product
■ do not touch tip of container to any surface to avoid contamination
■ replace cap after each use

■ avoid direct sunlight

DOSAGE AND ADMINISTRATION

external use only